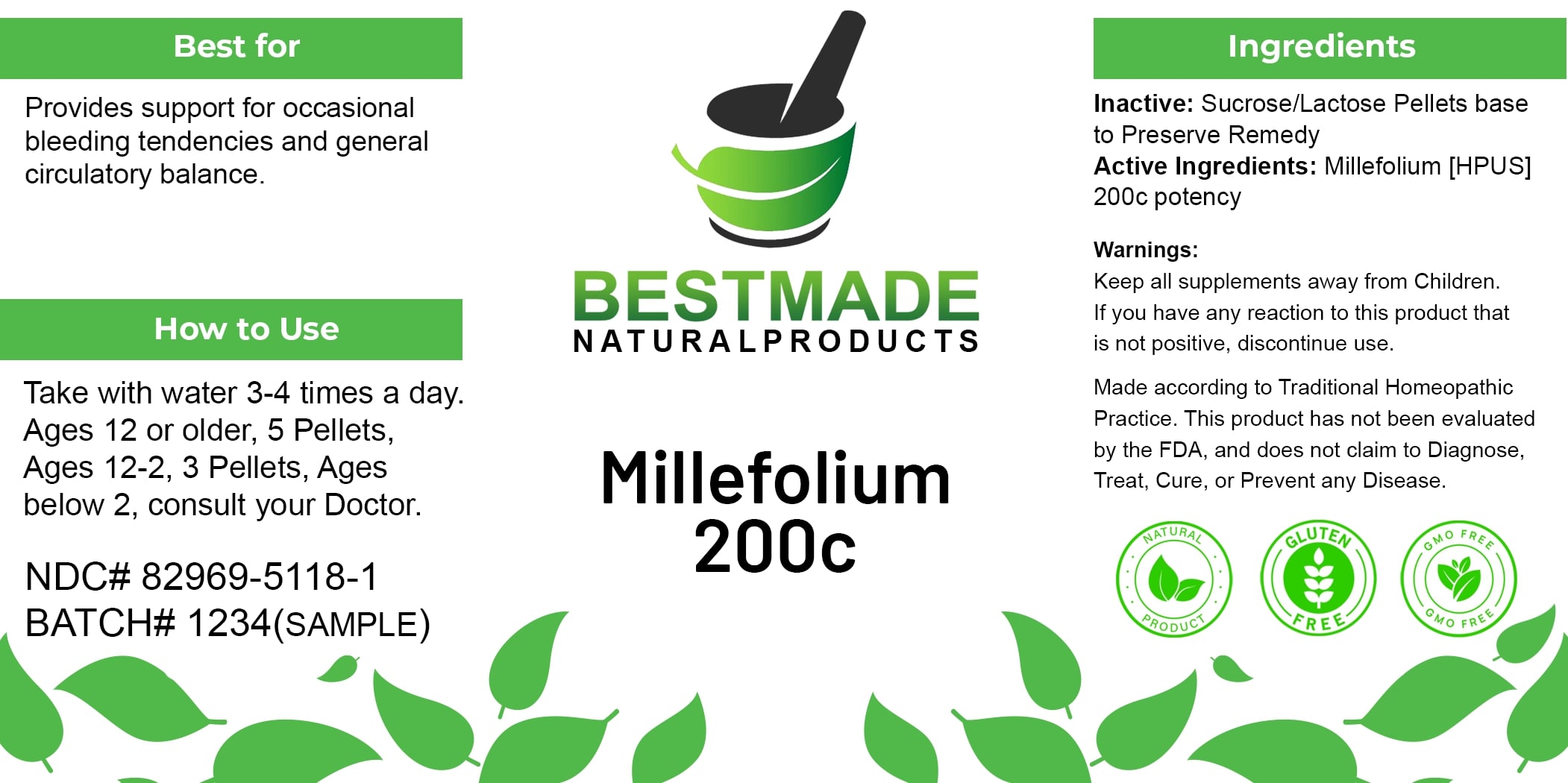 DRUG LABEL: Bestmade Natural Products Millefolium
NDC: 82969-5118 | Form: TABLET, SOLUBLE
Manufacturer: Bestmade Natural Products
Category: homeopathic | Type: HUMAN OTC DRUG LABEL
Date: 20241226

ACTIVE INGREDIENTS: ACHILLEA MILLEFOLIUM 200 [hp_C]/200 [hp_C]
INACTIVE INGREDIENTS: LACTOSE 200 [hp_C]/200 [hp_C]; SUCROSE 200 [hp_C]/200 [hp_C]

Millefolium

DOSAGE AND ADMINISTRATION

How to Use

Take with water 3-4 times a day. Ages 12 or older, 5 Pellets; Ages 12-3, 3 Pellets; Ages below 2, consult your Doctor.

INDICATIONS AND USAGE

Best for

Provides support for occasional bleeding tendencies and general circulatory balance.

PURPOSE

Best for

Provides support for occasional bleeding tendencies and general circulatory balance.

INACTIVE INGREDIENT

Ingredients

Inactive: Sucrose/Lactose Pellets base to Preserve Remedy

Active Ingredients: Millefolium [HPUS] 200c potency

Warnings:

Keep all supplements away from Children.

If you have any reaction to this product that is not positive, discontinue use.

Made according to Traditional Homeopathic Practice. This product has not been evaluated by the FDA, and does not claim to Diagnose, Treat, Cure, or Prevent any Disease.

Warnings:

Keep all supplements away from Children.

If you have any reaction to this product that is not positive, discontinue use.

Made according to Traditional Homeopathic Practice. This product has not been evaluated by the FDA, and does not claim to Diagnose, Treat, Cure, or Prevent any Disease.

Entire package label